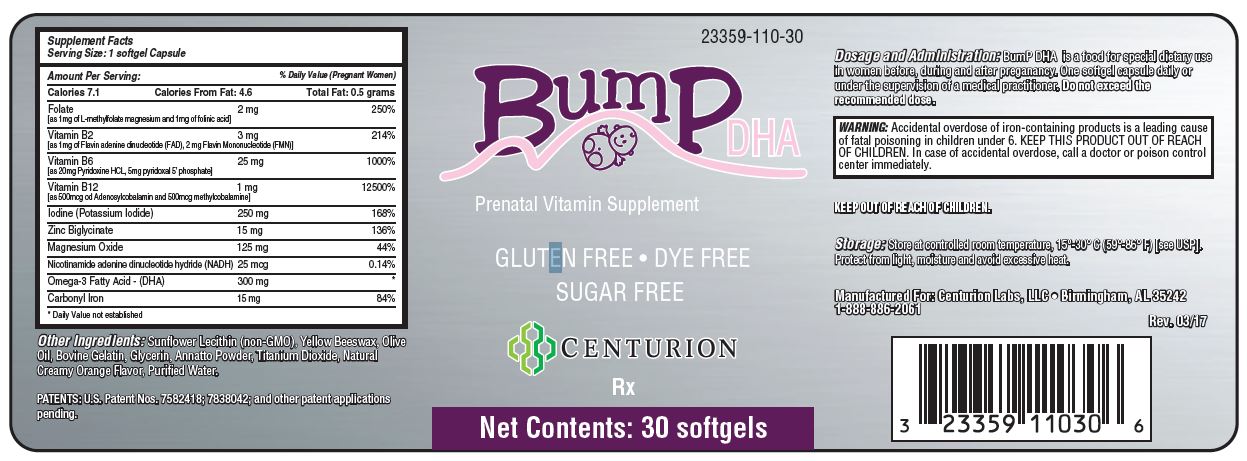 DRUG LABEL: BumP DHA
NDC: 23359-110 | Form: CAPSULE
Manufacturer: Centurion Labs, LLC
Category: other | Type: Dietary Supplement
Date: 20170412

ACTIVE INGREDIENTS: LEVOMEFOLATE MAGNESIUM 1 mg/1 1; LEUCOVORIN 1 mg/1 1; FLAVIN ADENINE DINUCLEOTIDE 1 mg/1 1; FLAVIN MONONUCLEOTIDE 2 mg/1 1; PYRIDOXINE HYDROCHLORIDE 20 mg/1 1; PYRIDOXAL PHOSPHATE ANHYDROUS 5 mg/1 1; COBAMAMIDE 500 mg/1 1; POTASSIUM IODIDE 250 ug/1 1; ZINC GLYCINATE 15 mg/1 1; MAGNESIUM OXIDE 125 mg/1 1; NADH 25 ug/1 1; OMEGA-3 FATTY ACIDS 300 mg/1 1; IRON PENTACARBONYL 15 mg/1 1
INACTIVE INGREDIENTS: LECITHIN, SUNFLOWER; YELLOW WAX; OLIVE OIL; GELATIN; GLYCERIN; ANNATTO; TITANIUM DIOXIDE; WATER

BumP DHA™

DESCRIPTION

BumP DHA is a food for special dietary use in women who are pregnant or lactating.

Supplement Facts Serving Size: 1 Softgel Capsule
Amount per Serving: |  | %Daily Value; (Pregnant Women)
Calories | 7.1
Calories from fat | 4.6
Total Fat | 0.5 grams | *
Folate [as 1mg of L-methylfolate magnesium and 1mg of folinic acid] | 2 mg | 250%
Vitamin B2; [as 1mg Flavin adenine dinucleotide (FAD), 2mg Flavin Mononucleotide (FMN)] | 3 mg | 214%
Vitamin B6 [as 20mg Pyridoxine HCL, 5mg pyridoxal 5’ phosphate] | 25mg | 1000%
Vitamin B12; [as 500mcg of Adenosylcobalamin and 500mcg methylcobalamine] | 1 mg | 12500%
Iodine (Potassium Iodide) | 250mcg | 168%
Zinc Biglycinate | 15mg | 136%
Magnesium Oxide | 125mg | 44%
Nicotinamide adenine dinucleotide hydride (NADH) | 25 mcg | 0.14%
Omega-3 Fatty Acid- (DHA) | 300mg | *
Carbonyl Iron | 15mg | 84%

*Daily Value not established

Other ingredients: Sunflower Lecithin (non-GMO), Yellow Beeswax, Olive Oil, Bovine Gelatin, Glycerin, Annatto Powder, Titanium Dioxide, Natural Creamy Orange Flavor, Purified Water.

Bump DHA™ is a food for special dietary use dispensed by prescription, for women who are preparing for pregnancy, are pregnant or for postnatal mothers. Bump DHA™ contains a proprietary blend of biologically active folate, vitamins, minerals and long-chain polyunsaturated fatty acids, derived from food sources.

This product is not an Orange Book product.

WARNINGS

WARNING: Ingestion of more than 3 grams of omega-3 fatty acids (such as ALA, EPA, and DHA) per day has been shown to have potential antithrombotic effects, including an increased bleeding time and International Normalized Ratio (INR). Administration of omega-3 fatty acids should be avoided in patients taking anticoagulants and in those known to have an inherited or acquired predisposition to bleeding. Exercise caution to ensure that the prescribed dosage of DHA does not exceed 1 gram (1000 mg) per day.

BOXED WARNING

WARNING: Accidental overdose of iron-containing products is a leading cause of fatal poisoning in children under 6. KEEP THIS PRODUCT OUT OF REACH OF CHILDREN. In case of accidental overdose, call a doctor or poison control center immediately.

RECOMMENDED USE

Bump DHA™ soft gels are food for special dietary use administered under the supervision of a medical practitioner, for women who are preparing for pregnancy, pregnant or are postnatal.

The usual adult dose is one soft gel daily or as directed by a medical professional.

If you are pregnant inform your doctor, or if nursing, your child’s doctor that you are using this product.

Bump DHA™ is contraindicated in patients with known hypersensitivity to any of the ingredients.

HOW SUPPLIED

BumP DHA™ is supplied as oval, annatto-colored soft gelatin capsules with "B-DHA" on one side. In bottles of 30 softgels 23359-110-30* and bottles of 90 softgels 23359-110-90*

BumP DHA™ is also supplied to licensed healthcare practitioners as samples in bottles of 5 softgels, 23359-110-05* Professional samples- not for sale.

Centurion Labs, LLC does not represent these product codes to be National Drug Codes (NDC). Product codes are formatted according to standard industry practice, to meet the formatting requirements of pharmacy and health insurance computer systems.

STORAGE

Store at controlled room temperature 15°-30°C (59°-86°F) [See USP]. Protect from light, moisture, and excessive heat.

Administer under the supervision of a medical practitioner.

KEEP THIS PRODUCT OUT OF REACH OF CHILDREN.

HEALTH CLAIM

GLUTEN FREE
SUGAR FREE
DYE FREE

Manufactured for:
CENTURION LABS, LLC
Birmingham, AL 35242
1-888-886-2061

MADE IN CANADA

PATENTS: US Patent Nos. 7582418, 7838042 and other patent applications pending.

TRADEMARKS: Bump DHA™ is a trademark of Centurion Labs, LLC (Birmingham,
Alabama, USA). L-methylfolate magnesium is under license from Viva Pharmaceutical Inc. (Canada).

Rev. 3/17